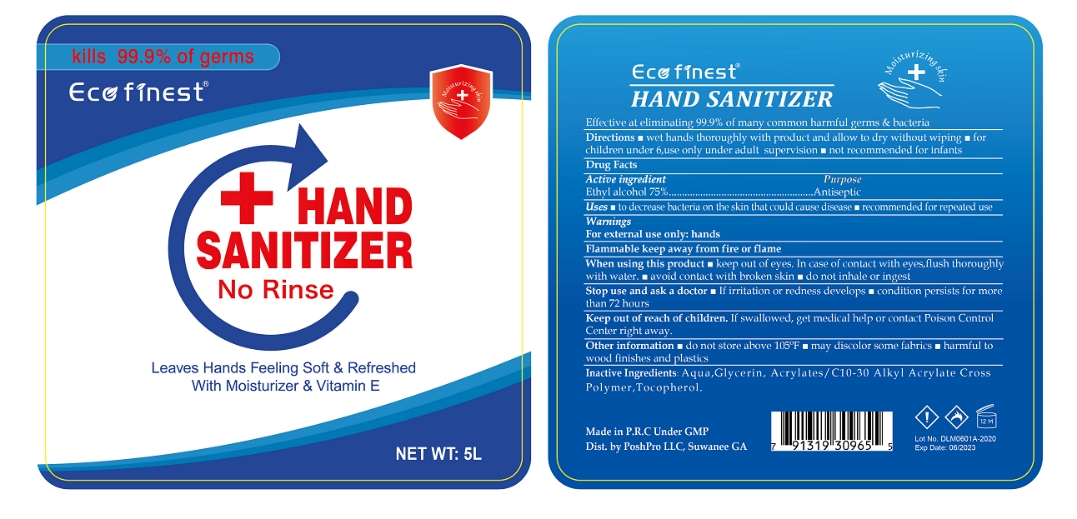 DRUG LABEL: Hand sanitizer
NDC: 55453-005 | Form: GEL
Manufacturer: Guangzhou Yikang Biotechnology Co., Ltd.
Category: otc | Type: HUMAN OTC DRUG LABEL
Date: 20200908

ACTIVE INGREDIENTS: ALCOHOL 3750 mL/5000 mL
INACTIVE INGREDIENTS: GLYCERIN; WATER; CARBOMER INTERPOLYMER TYPE A (55000 CPS); TOCOPHEROL

DOSAGE AND ADMINISTRATION

Do not store above 105°F.

INACTIVE INGREDIENT

Aqua, Glycerin, Acrylates/C10-30 Alkyl Acrylate Cross Polymer, Tocopherol

INDICATIONS AND USAGE

wet hands thoroughly with product and allow to dry without wiping .

ACTIVE INGREDIENT

Ethyl Alcohol

keep out of reach of children

PURPOSE

Disinfection

Sterilization
No Rinseing

WARNINGS

For external use only: hands.Flammable keep away from fire or flame